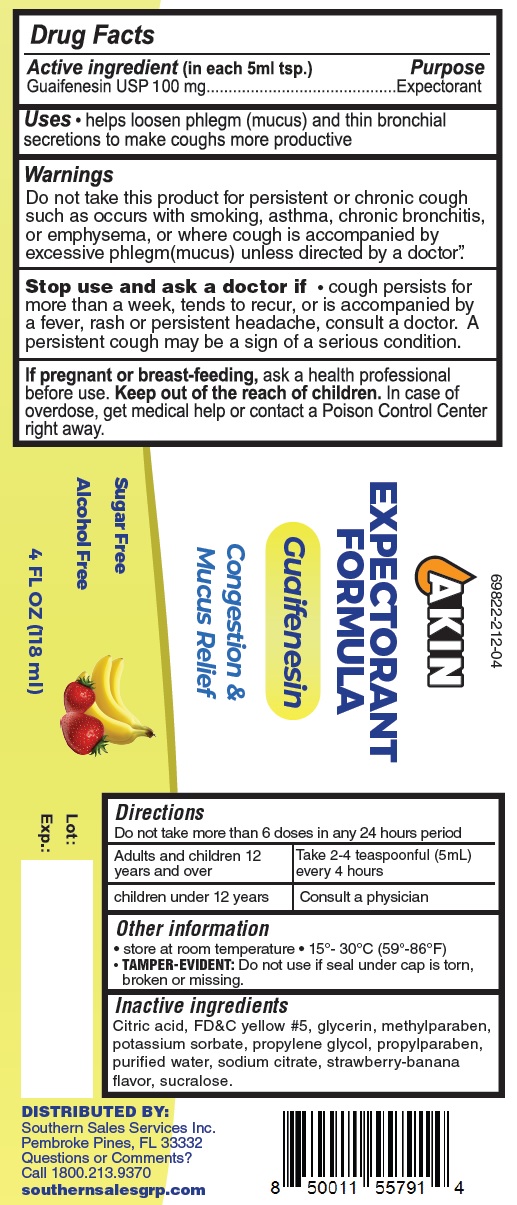 DRUG LABEL: Akin Expectorant Formula Strawberry Banana
NDC: 69822-212 | Form: LIQUID
Manufacturer: Southern Sales & Service, Inc.
Category: otc | Type: HUMAN OTC DRUG LABEL
Date: 20231129

ACTIVE INGREDIENTS: GUAIFENESIN 100 mg/5 mL
INACTIVE INGREDIENTS: CITRIC ACID MONOHYDRATE; FD&C YELLOW NO. 5; GLYCERIN; METHYLPARABEN; POTASSIUM SORBATE; PROPYLENE GLYCOL; PROPYLPARABEN; WATER; SODIUM CITRATE; SUCRALOSE

Akin Expectorant Formula (Strawberry - Banana)

Active ingredient (in each 5ml tsp.)

Guaifenesin USP 100 mg

Purpose

Expectorant

Uses

• helps loosen phlegm (mucus) and thin bronchial secretions to make coughs more productive

Warnings

Do not take this product for persistent or chronic cough such as occurs with smoking, asthma, chronic bronchitis, or emphysema, or where cough is accompanied by excessive phlegm(mucus) unless direct by a doctor."

Stop use and ask a doctor if

• cough persists for more than a week, tends to recur, or is accompanied by a fever, rash or persistant headache, consult a doctor. A persistent cough may be a sign of a serious condition.

If pregnant or beast-feeding,

ask a health professional before use.

Keep out of reach of children.

In case of overdose, get medical help or contact a Poison Control Center right away.

Directions

Do not take more than 6 doses in any 24 hours period

Adults and children 12 years and over | Take 2-4 teaspoonful (5mL) every 4 hours
Children under 12 years | Consult a physician

Other information

• store at room temperature • 15°-30°C (59°-86°F)

Do not use if seal under cap is torn, broken or missing. TAMPER-EVIDENT:

Inactive ingredients

Citric acid, FD&C yellow #5, glycerin, methylparaben, potassium sorbate, propylene glycol, propylparaben, purified water, sodium citrate, strawberry-banana flavor, sucralose.